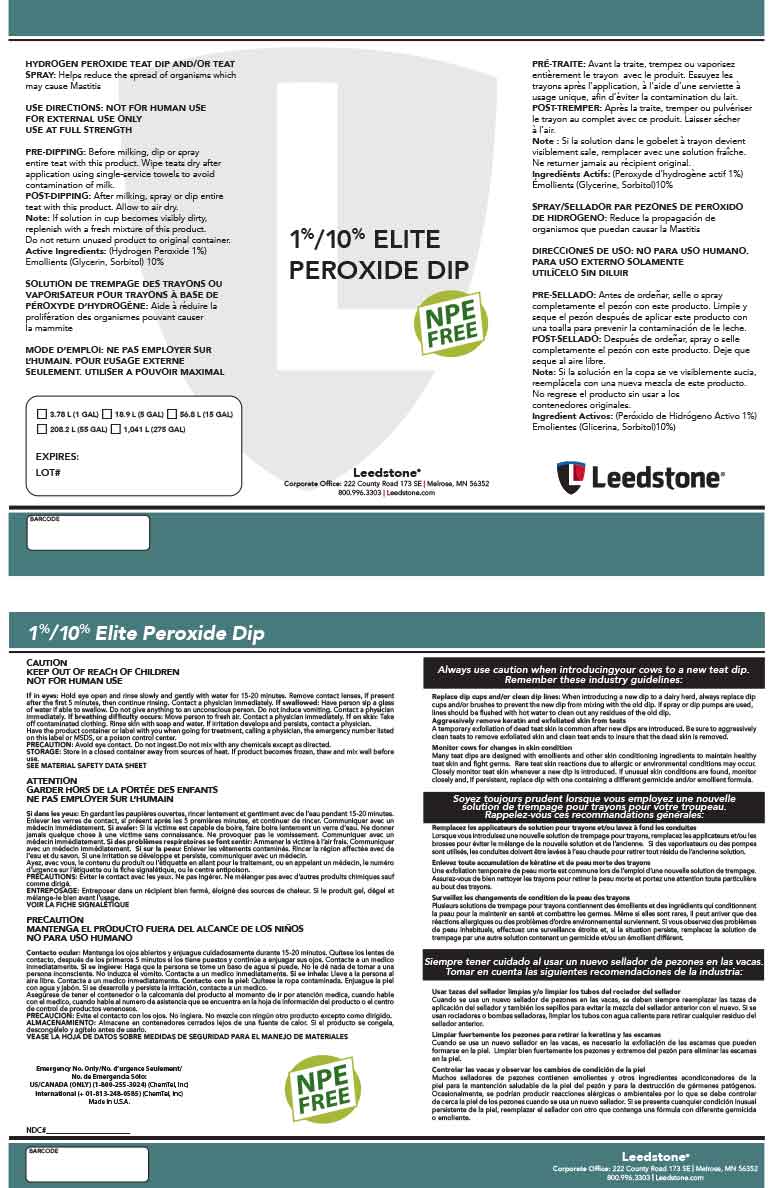 DRUG LABEL: 1%/10% Elite Peroxide Dip
NDC: 48106-2043 | Form: LIQUID
Manufacturer: BOUMATIC, LLC
Category: animal | Type: OTC ANIMAL DRUG LABEL
Date: 20221202

ACTIVE INGREDIENTS: HYDROGEN PEROXIDE 1.224 g/100 g
INACTIVE INGREDIENTS: GLYCERIN 6 g/100 g; SORBITOL 2.8 g/100 g; UREA 0.2 g/100 g; DODECYL BENZENE SULFONATE DIETHANOLAMINE (MIXED ISOMERS) 1 g/100 g; WATER 88.776 g/100 g

1%/10% Elite Peroxide Dip

Summary of effectiveness

Helps reduce the spread of organisms which may
cause Mastitis

Instructions for Use

USE DIRECTIONS: NOT FOR HUMAN USE
FOR EXTERNAL USE ONLY
USE AT FULL STRENGTH
PRE-DIPPING: Before milking, dip entire teat with
this product. Wipe teats dry after application using
single-service towels to avoid contamination of milk.
POST-DIPPING: After milking, dip entire teat with this
product. Allow to air dry.
Note: If solution in cup becomes visibly dirty,
replenish with a fresh mixture of this product.
Do not return unused product to original container.

Safe Handling

CAUTION
KEEP OUT OF REACH OF CHILDREN
NOT FOR HUMAN USE

General Precautions

Avoid eye contact. Do not ingest.Do not mix with any chemicals except as directed.

NOT FOR HUMAN USE
FOR EXTERNAL USE ONLY
USE AT FULL STRENGTH

Storage

Store in a closed container away from sources of heat. If product becomes frozen, thaw and mix well before
use.

label